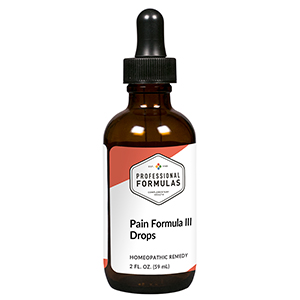 DRUG LABEL: Pain Formula III Drops
NDC: 63083-2091 | Form: LIQUID
Manufacturer: Professional Complementary Health Formulas
Category: homeopathic | Type: HUMAN OTC DRUG LABEL
Date: 20190815

ACTIVE INGREDIENTS: VALERIAN 1 [hp_X]/59 mL; DIOSCOREA VILLOSA TUBER 3 [hp_X]/59 mL; POTASSIUM IODIDE 3 [hp_X]/59 mL; PULSATILLA MONTANA WHOLE 4 [hp_X]/59 mL; STRYCHNOS IGNATII SEED 5 [hp_X]/59 mL; OXALIC ACID 6 [hp_X]/59 mL; TOXICODENDRON PUBESCENS LEAF 6 [hp_X]/59 mL
INACTIVE INGREDIENTS: ALCOHOL; WATER

C91

ACTIVE INGREDIENTS

Valeriana officinalis 1X
Dioscorea villosa 3X
Kali iodatum 3X
Pulsatilla 4X
Ignatia amara 5X
Oxalicum acidum 6X
Rhus toxicodendron 6X

QUESTIONS

Professional Formulas

PO Box 2034 Lake Oswego, OR 97035

INDICATIONS

For the temporary relief of minor aches or pain, particularly when improved by movement or stretching.*

PURPOSE

*Claims based on traditional homeopathic practice, not accepted medical evidence. Not FDA evaluated.

WARNINGS

In case of overdose, get medical help or contact a poison control center right away.

Keep out of the reach of children.

PREGNANCY OR BREAST FEEDING

If pregnant or breastfeeding, ask a healthcare professional before use.

DIRECTIONS

Place drops under tongue 30 minutes before/after meals. Adults and children 12 years and over: Take 10 drops up to 3 times per day for up to 6 weeks. For immediate onset of symptoms, take 10 to 15 drops every 15 minutes up to 3 hours. For less severe symptoms, take 10-15 drops hourly up to 8 hours. Consult a physician for use in children under 12 years of age.

OTHER INFORMATION

Tamper resistant. If seal is broken, do not use. After opening, close container tightly and store at room temperature away from heat.

INACTIVE INGREDIENTS

20% ethanol, purified water.

LABEL

Est 1985

Professional Formulas

Complementary Health

Pain Formula III Drops

Homeopathic Remedy

2 FL. OZ. (59 mL)